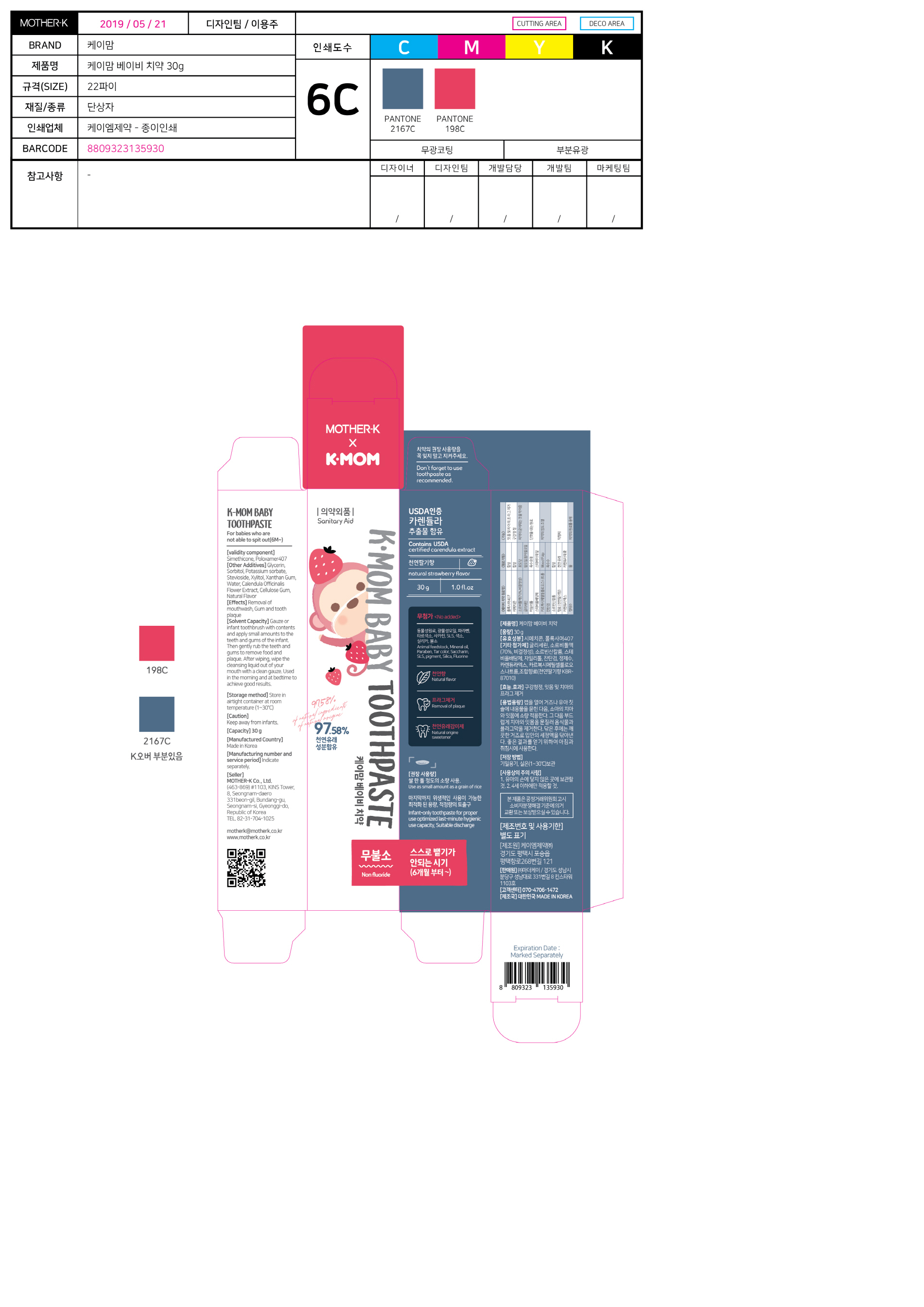 DRUG LABEL: K-MOM Baby Tooth
NDC: 73429-0002 | Form: PASTE, DENTIFRICE
Manufacturer: MOTHER-K CO.,LTD
Category: otc | Type: HUMAN OTC DRUG LABEL
Date: 20191126

ACTIVE INGREDIENTS: POLOXAMER 407 2 g/100 g
INACTIVE INGREDIENTS: XYLITOL; WATER

ACTIVE INGREDIENT

Poloxamer 407, Simethicone

PURPOSE

For dental care

Keep out of reach of children

INDICATIONS AND USAGE

Use as small amount as a grain of rice.

WARNINGS

Keep away from infants.

INACTIVE INGREDIENT

Sorbitol, Water, Xylitol, Stevioside, Cellulose Gum, Xanthan Gum, Potassium Sorbate, Etc.

DOSAGE AND ADMINISTRATION

For dental use only